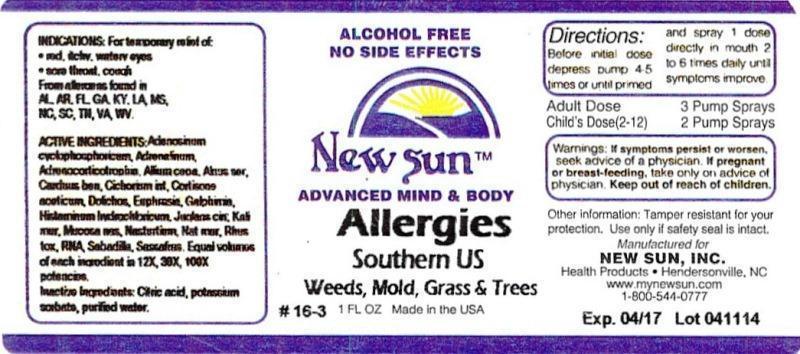 DRUG LABEL: Allergies Southern US
NDC: 66579-0035 | Form: LIQUID
Manufacturer: New Sun Inc.
Category: homeopathic | Type: HUMAN OTC DRUG LABEL
Date: 20140730

ACTIVE INGREDIENTS: ADENOSINE CYCLIC PHOSPHATE 12 [hp_X]/29 mL; EPINEPHRINE 12 [hp_X]/29 mL; CORTICOTROPIN 12 [hp_X]/29 mL; ONION 12 [hp_X]/29 mL; ALNUS SERRULATA BARK 12 [hp_X]/29 mL; CENTAUREA BENEDICTA 12 [hp_X]/29 mL; CHICORY ROOT 12 [hp_X]/29 mL; CORTISONE ACETATE 12 [hp_X]/29 mL; MUCUNA PRURIENS FRUIT TRICHOME 12 [hp_X]/29 mL; EUPHRASIA STRICTA 12 [hp_X]/29 mL; GALPHIMIA GLAUCA FLOWERING TOP 12 [hp_X]/29 mL; HISTAMINE DIHYDROCHLORIDE 12 [hp_X]/29 mL; JUGLANS CINEREA BRANCH BARK/ROOT BARK 12 [hp_X]/29 mL; POTASSIUM CHLORIDE 12 [hp_X]/29 mL; SUS SCROFA NASAL MUCOSA 12 [hp_X]/29 mL; NASTURTIUM OFFICINALE 12 [hp_X]/29 mL; SODIUM CHLORIDE 12 [hp_X]/29 mL; TOXICODENDRON PUBESCENS LEAF 12 [hp_X]/29 mL; SACCHAROMYCES CEREVISIAE RNA 12 [hp_X]/29 mL; SCHOENOCAULON OFFICINALE SEED 12 [hp_X]/29 mL; SASSAFRAS ALBIDUM ROOT BARK 12 [hp_X]/29 mL
INACTIVE INGREDIENTS: CITRIC ACID MONOHYDRATE; POTASSIUM SORBATE; WATER

Allergies Southern US

DOSAGE AND ADMINISTRATION

Directions: Before initial dose depress pump 4-5 times or until primed and spray 1 dose directly in mouth 2 to 6 times daily until symptoms improve.

Adult Dose: 3 Pump Sprays

Child's Dose (2-12): 2 Pump Sprays

WARNINGS

Warnings: If symptoms persist or worsen, seek advice of physician. If pregnant or breast-feeding, take only on advice of physician.

Keep out of reach of children.

Other information: Tamper resistant for your protection. Use only if safety seal is intact.

PURPOSE

Indications:For temporary relief of: •red, itchy, watery eyes •sore throat, cough

From allergens found in AL, AR, FL, GA, KY, LA, MS, NC, SC, TN, VA, WV.

ACTIVE INGREDIENT

Active Ingredients: Adenosinun cyclophosphoricum, Adrenalinum, Adrenocorticotrophin, Allium cepa, Alnus serrulata, Carduus benedictus, Cichorium intybus, Cortisone aceticum, Dolichos pruriens, Euphrasia officinalis, Galphimia glauca, Histaminum hydrochloricum, Juglans cinerea, Kali muriaticum, Mucosa nasalis suis, Nasturtium aquaticum, Natrum muriaticum, Rhus toxicodendron, RNA, Sabadilla, Sassafras officinale. Equal volumes of each ingredient in 12X, 30X, 100X potencies.

Inactive Ingredient: Citric acid, potassium sorbate, purified water.

Indications: For temporary relief of:

- red, itchy, watery eyes
- sore throat, cough

From allergens found in AL, AR, FL, GA, KY, LA, MS, NC, SC, TN, VA, WV.